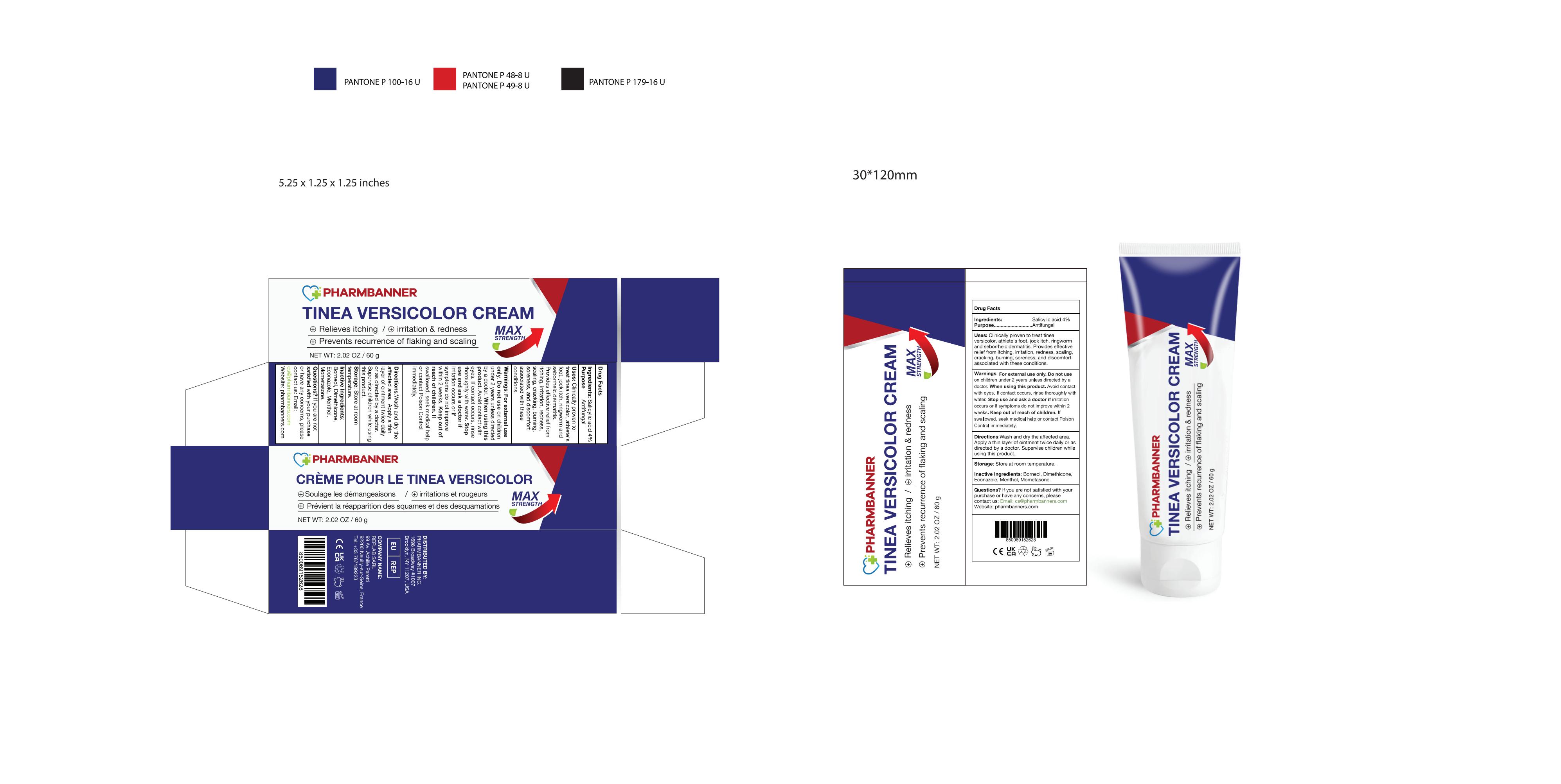 DRUG LABEL: PHARMBANNER Tinea Versicolor Cream
NDC: 83818-020 | Form: CREAM
Manufacturer: Shenzhen Xinxin Yunhai Technology Co., Ltd.
Category: otc | Type: HUMAN OTC DRUG LABEL
Date: 20260212

ACTIVE INGREDIENTS: SALICYLIC ACID 4 g/100 g
INACTIVE INGREDIENTS: MOMETASONE; ECONAZOLE; MENTHOL; DIMETHICONE; BORNEOL

83818-020 Update Manufacturer

Active Ingredient

Salicylic acid 4%

Purpose

Antifungal

Use

Clinically proven to treat tinea versicolor, athlete's foot, jock itch, ringworm and seborrheic dermatitis.
Provides effective relief from itching, irritation, redness, scaling, cracking, burning, soreness, and discomfort associated with these conditions.

Warnings

For external use only.

Do not use

on children under 2 years unless directed by a doctor.

When Using

Avoid contact with eyes. If contact occurs, rinse thoroughly with water.

Stop Use

if irritation occurs or if symptoms do not improve within 2 weeks.

Ask Doctor

if irritation occurs or if symptoms do not improve within 2 weeks.

Keep Out Of Reach Of Children

If swallowed, seek medical help or contact Poison Control immediately.

Directions

Wash and dry the affected area.
Apply a thin layer of ointment twice daily or as directed by a doctor. Supervise children while using this product.

Other information

Store at room temperature.

Inactive ingredients

Borneol；Dimethicone；Econazole；Menthol；Mometasone

Questions

Please contact us:
Email: cs@pharmbanners.com
Website: pharmbanners.com